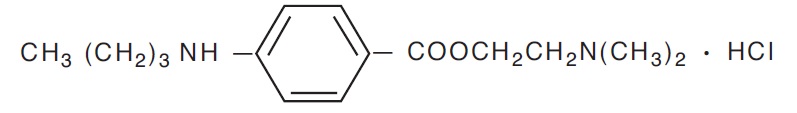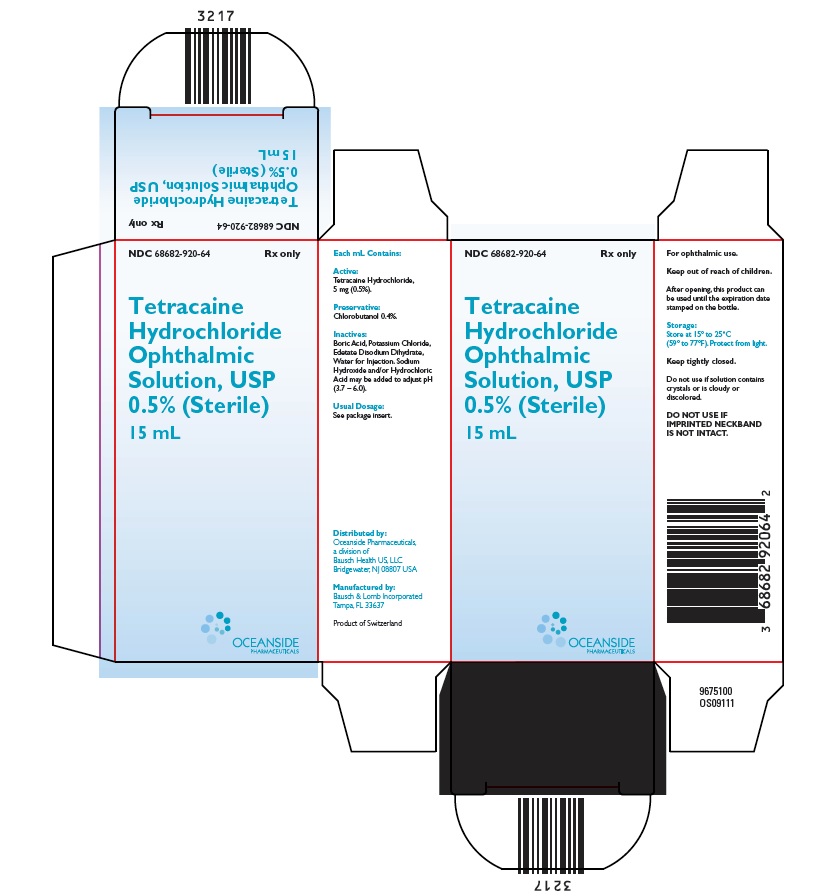 DRUG LABEL: Tetracaine Hydrochloride
NDC: 68682-920 | Form: SOLUTION/ DROPS
Manufacturer: Oceanside Pharmaceuticals
Category: prescription | Type: HUMAN PRESCRIPTION DRUG LABEL
Date: 20260121

ACTIVE INGREDIENTS: TETRACAINE HYDROCHLORIDE 5 mg/1 mL
INACTIVE INGREDIENTS: CHLOROBUTANOL; BORIC ACID; POTASSIUM CHLORIDE; EDETATE DISODIUM; WATER; SODIUM HYDROXIDE; HYDROCHLORIC ACID

HIGHLIGHTS OF PRESCRIBING INFORMATION

These highlights do not include all the information needed to use TETRACAINE HYDROCHLORIDE OPHTHALMIC SOLUTION, USP 0.5%safely and effectively. See full prescribing information for TETRACAINE HYDROCHLORIDE OPHTHALMIC SOLUTION, USP 0.5%.
TETRACAINE HYDROCHLORIDE OPHTHALMIC SOLUTION, USP 0.5%, for topical ophthalmic use
Initial U.S. Approval: 1965

RECENT MAJOR CHANGES

1. Warnings and Precautions (5.4) 2/2022

1 INDICATIONS AND USAGE

Tetracaine Hydrochloride Ophthalmic Solution, USP 0.5%, is an ester local anesthetic indicated for procedures requiring a rapid and short-acting topical ophthalmic anesthetic. (1)

2 DOSAGE AND ADMINISTRATION

One drop topically in the eye(s) as needed. (2)

3 DOSAGE FORMS AND STRENGTHS

Ophthalmic solution containing 0.5% tetracaine hydrochloride. (3)

4 CONTRAINDICATIONS

Tetracaine Hydrochloride Ophthalmic Solution, USP 0.5% should not be used in patients with a history of hypersensitivity to any component of this preparation. (4)

5 WARNINGS AND PRECAUTIONS

- Do not use intracamerally since use may damage corneal endothelial cells. (5.1)
- Prolonged use or abuse may lead to corneal epithelial toxicity and may manifest as epithelial defects which may progress to permanent corneal damage. (5.2)
- Patients should not touch the eye for at least 10-20 minutes after using anesthetic as accidental injuries can occur due to insensitivity of the eye. (5.3)
- For Administration by Healthcare Provider: Tetracaine Hydrochloride Ophthalmic Solution, USP 0.5% is not intended for patient self-administration. (5.4)

6 ADVERSE REACTIONS

Ocular adverse events: transient stinging, burning, conjunctival redness, eye irritation, eye pain, ocular discomfort. (6)

To report SUSPECTED ADVERSE REACTIONS, contactOceanside Pharmaceuticals at 1-800-321-4576 or FDA at 1-800-FDA-1088 or www.fda.gov/medwatch.

FULL PRESCRIBING INFORMATION

1 INDICATIONS AND USAGE

Tetracaine Hydrochloride Ophthalmic Solution, USP 0.5% is indicated for procedures requiring a rapid and short-acting topical ophthalmic anesthetic.

2 DOSAGE AND ADMINISTRATION

One drop topically in the eye(s) as needed.

3 DOSAGE FORMS AND STRENGTHS

Tetracaine Hydrochloride Ophthalmic Solution, USP 0.5% is a clear, colorless, ophthalmic solution containing 0.5% w/v tetracaine hydrochloride equivalent to tetracaine 0.44% w/v.

4 CONTRAINDICATIONS

Tetracaine Hydrochloride Ophthalmic Solution, USP 0.5% should not be used in patients with a history of hypersensitivity to any component of this preparation.

5 WARNINGS AND PRECAUTIONS

5.1 Corneal Injury with Intracameral Use

Not for injection or intraocular use. Do not use intracamerally because use of Tetracaine Hydrochloride Ophthalmic Solution, USP 0.5% may lead to damage of the corneal endothelial cells.

5.2 Corneal Toxicity

Prolonged use or abuse may lead to corneal epithelial toxicity and may manifest as epithelial defects which may progress to permanent corneal damage.

5.3 Corneal Injury Due to Insensitivity

Patients should not touch the eye for at least 10-20 minutes after using anesthetic as accidental injuries can occur due to insensitivity of the eye.

5.4 For Administration by Healthcare Provider

Tetracaine Hydrochloride Ophthalmic Solution, USP 0.5% is indicated for administration under the direct supervision of a healthcare provider. Tetracaine Hydrochloride Ophthalmic Solution, USP 0.5% is not intended for patient self-administration [see Warnings and Precautions(5.2)].

6 ADVERSE REACTIONS

The following serious ocular adverse reactions are described elsewhere in the labeling:

- Corneal Injury with Intracameral Use [see Warnings and Precautions (5.1)]
- Corneal Toxicity [see Warnings and Precautions (5.2)]
- Corneal Injury Due to Insensitivity [see Warnings and Precautions (5.3)]

The following adverse reactions have been identified following use of Tetracaine Hydrochloride Ophthalmic Solution, USP 0.5%. Because these reactions are reported voluntarily from a population of uncertain size, it is not always possible to reliably estimate their frequency or establish a causal relationship to drug exposure.

Ocular Adverse Reactions

Transient stinging, burning, and conjunctival redness, eye irritation, eye pain, ocular discomfort.

8 USE IN SPECIFIC POPULATIONS

8.1 Pregnancy

Risk Summary

There are no adequate and well-controlled studies with Tetracaine Hydrochloride Ophthalmic Solution, USP 0.5% in pregnant women. Animal developmental and reproductive toxicity studies with tetracaine hydrochloride have not been reported in the published literature.

8.2 Lactation

Risk Summary

There are no data to assess whether Tetracaine Hydrochloride Ophthalmic Solution, USP 0.5% is excreted in human milk or to assess its effects on milk production/excretion. The developmental and health benefits of breastfeeding should be considered along with the mother’s clinical need for Tetracaine Hydrochloride Ophthalmic Solution, USP 0.5% and any potential adverse effects on the breastfed child from Tetracaine Hydrochloride Ophthalmic Solution, USP 0.5%.

8.3 Females and Males of Reproductive Potential

No human data on the effect of Tetracaine Hydrochloride Ophthalmic Solution, USP 0.5% on fertility are available.

8.4 Pediatric Use

Safety of Tetracaine Hydrochloride Ophthalmic Solution, USP 0.5% in the pediatric population has been demonstrated in clinical trials. Efficacy of Tetracaine Hydrochloride Ophthalmic Solution, USP 0.5% for use in pediatric patients has been extrapolated from adequate and well controlled clinical trials in the adult population.

8.5 Geriatric Use

No overall differences in safety or effectiveness of Tetracaine Hydrochloride Ophthalmic Solution, USP 0.5% have been observed between elderly and younger patients.

10 OVERDOSAGE

Prolonged use of a topical ocular anesthetic including Tetracaine Hydrochloride Ophthalmic Solution, USP 0.5% may produce permanent corneal opacification and ulceration with accompanying visual loss.

11 DESCRIPTION

Tetracaine Hydrochloride Ophthalmic Solution, USP 0.5% is a sterile, clear, colorless, topical local anesthetic for ophthalmic use only containing tetracaine hydrochloride as the active pharmaceutical ingredient.

Tetracaine hydrochloride is chemically designated as benzoic acid, 4-(butylamino)-, 2-(dimethylamino) ethyl ester, monohydrochloride. Its chemical formula is C15H24N2O2● HCl and it is represented by the chemical structure:

Tetracaine hydrochloride is a fine, white, crystalline, odorless powder with a molecular weight of 300.82

Active ingredient: tetracaine hydrochloride 0.5% w/v (equivalent to 0.44% w/v tetracaine)

Preservative: chlorobutanol 0.4%

Inactive ingredients: boric acid, potassium chloride, edetate disodium dihydrate, water for injection. Sodium hydroxide and/or hydrochloric acid may be added to adjust pH (3.7 – 6.0).

12 CLINICAL PHARMACOLOGY

12.1 Mechanism of Action

Tetracaine blocks sodium ion channels required for the initiation and conduction of neuronal impulses thereby affecting local anesthesia.

12.3 Pharmacokinetics

The systemic exposure to tetracaine following topical ocular administration of Tetracaine Hydrochloride Ophthalmic Solution, USP 0.5% has not been studied. Tetracaine hydrochloride is metabolized by plasma pseudocholinesterases and nonspecific esterases in ocular tissues.

13 NONCLINICAL TOXICOLOGY

13.1 Carcinogenesis, Mutagenesis, Impairment of Fertility

Studies to assess the genotoxicity of tetracaine hydrochloride have not been reported in the published literature. Long-term animal studies have not been conducted to evaluate the carcinogenic potential of tetracaine hydrochloride. Animal studies to assess the effects of tetracaine hydrochloride on fertility have not been reported in the published literature.

14 CLINICAL STUDIES

Topical administration of Tetracaine Hydrochloride Ophthalmic Solution, USP 0.5% results in localized temporary anesthesia. The maximum effect is achieved within 10–20 seconds after instillation, with efficacy lasting 10–20 minutes. Duration of effect can be extended with repeated dosing [see Warnings and Precautions (5.2) and Overdosage(10)] .

16 HOW SUPPLIED/STORAGE AND HANDLING

Tetracaine Hydrochloride Ophthalmic Solution, USP 0.5% is supplied as a sterile, aqueous, topical ophthalmic solution in a low-density polyethylene plastic dropper bottle with a low-density polyethylene dropper tip and white polypropylene cap in the following sizes:

2. NDC 68682-920-64 15 mL in a 15 mL Bottle
4. NDC 68682-920-05 5 mL in a 7.5 mL Bottle

After opening, this product can be used until the expiration date stamped on the bottle.

Storage: Store at 15° to 25°C (59° to 77°F). Protect from light. Do not use if solution contains crystals, cloudy, or discolored.

17 PATIENT COUNSELING INFORMATION

Eye Care Precaution

Do not touch the dropper tip to any surface as this may contaminate the solution.

Advise patients that, due to the effect of the anesthetic, their eyes will be insensitive for up to 20 minutes and that care should be taken to avoid accidental injuries.

Distributed by:
Oceanside Pharmaceuticals, a division of
Bausch Health US, LLC
Bridgewater, NJ 08807 USA
Manufactured by:
Bausch & Lomb Incorporated
Tampa, FL 33637 USA
© 2022 Bausch Health Companies Inc. or its affiliates
9675203 (Folded)
9675303 (Flat)

PACKAGE/LABEL PRINCIPAL DISPLAY PANEL

NDC68682-920-64

Rx only

Tetracaine
Hydrochloride

Ophthalmic
Solution, USP
0.5% (Sterile)
15 mL

OCEANSIDE
PHARMACEUTICALS